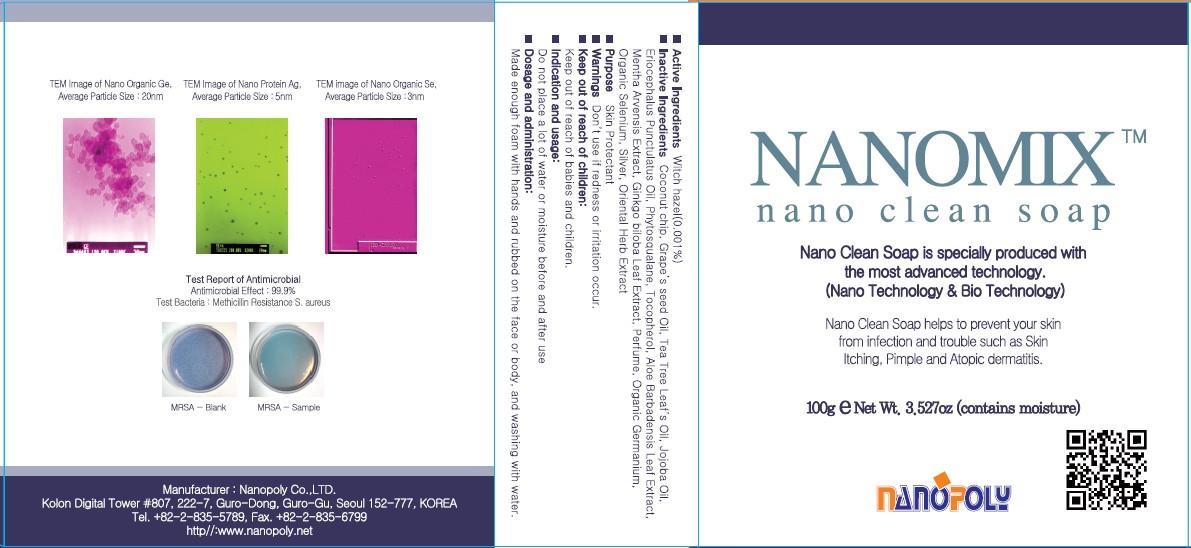 DRUG LABEL: NANOMIX NANO CLEAN
NDC: 54170-100 | Form: SOAP
Manufacturer: NANOPOLY CO., LTD.
Category: otc | Type: HUMAN OTC DRUG LABEL
Date: 20121226

ACTIVE INGREDIENTS: Witch hazel 0.001 g/100 g
INACTIVE INGREDIENTS: COCONUT; GRAPE SEED OIL; JOJOBA OIL; ALOE VERA LEAF

ACTIVE INGREDIENT

Active Ingredients: Witch hazel (0.001%)

INACTIVE INGREDIENT

Inactive Ingredients:
Coconut chip, Grape’s seed Oil, Tea Tree Leaf’s Oil, Jojoba Oil, Eriocephalus Punctulatus Oil, Phytosqualane, Tocopherol, Aloe Barbadensis Leaf Extract, Mentha Arvensis Extract, Ginkgo biloba Leaf Extract, Perfume, Organic Germanium, Organic Selenium, Silver, Oriental Herb Extract

PURPOSE

Purpose: Skin Protectant

WARNINGS

Warnings: Don't use if redness or irritation occur.

KEEP OUT OF REACH OF CHILDREN

Keep out of reach of babies and children.

INDICATIONS AND USAGE

Indication and usage:
Do not place a lot of water or moisture before and after use.

DOSAGE AND ADMINISTRATION

Made enough foam with hands and rubbed on the face or body, and washing with water.